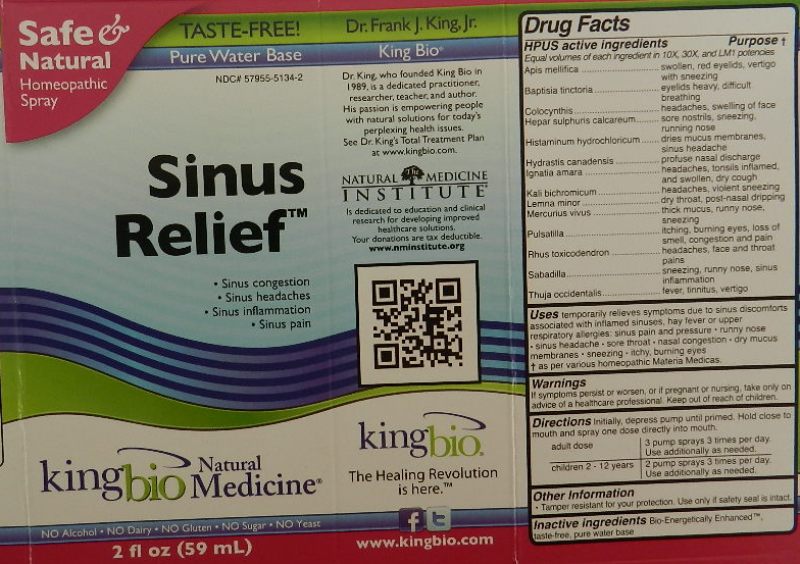 DRUG LABEL: Sinus Relief
NDC: 57955-5134 | Form: LIQUID
Manufacturer: King Bio Inc
Category: homeopathic | Type: HUMAN OTC DRUG LABEL
Date: 20111021

ACTIVE INGREDIENTS: APIS MELLIFERA 10 [hp_X]/59 mL; BAPTISIA TINCTORIA ROOT 10 [hp_X]/59 mL; CITRULLUS COLOCYNTHIS FRUIT PULP 10 [hp_X]/59 mL; CALCIUM SULFIDE 10 [hp_X]/59 mL; HISTAMINE DIHYDROCHLORIDE 10 [hp_X]/59 mL; GOLDENSEAL 10 [hp_X]/59 mL; STRYCHNOS IGNATII SEED 10 [hp_X]/59 mL; POTASSIUM DICHROMATE 10 [hp_X]/59 mL; LEMNA MINOR 10 [hp_X]/59 mL; MERCURY 10 [hp_X]/59 mL; PULSATILLA VULGARIS 10 [hp_X]/59 mL; TOXICODENDRON PUBESCENS LEAF 10 [hp_X]/59 mL; SCHOENOCAULON OFFICINALE SEED 10 [hp_X]/59 mL; THUJA OCCIDENTALIS LEAFY TWIG 10 [hp_X]/59 mL
INACTIVE INGREDIENTS: WATER

Sinus Relief

OTC Active Ingredient

HPUS active ingredients

Equal volumes of each ingredient in 10X, 30X, and LM1 potencies

Apis mellifica

Baptisia tinctoria

Colocynthis

Hepar sulphuris calcareum

Histaminum hydrochloricum

Hydrastis canadensis

Ignatia amara

Kali bichromicum

Lemna minor

Mercurius vivus

Pulsatilla

Rhus toxicodendron

Sabadilla

Thuja occidentalis

Reference image sinus.jpg

Inactive Ingredient

Bio-Energetically Enhanced, taste free, pure water base.

Reference image sinus.jpg

Dosage and Administration

Directions: Initially, depress pump until primed. Hold close to mouth and spray one dose directly into mouth.

Adult dose: 3 pump sprays 3 times per day. Use additionally as needed.

Children 2-12 years: 2 pump sprays 3 times per day. Use additionally as needed.

Reference image sinus.jpg

Purpose

HPUS active ingredients Purpose

Apis mellifica............................swollen, red eyelids, vertigo with sneezing

Baptisia tinctoria.......................eyelids heavy, difficult breathing

Colocynthis..............................headaches, swelling of face

Hepar sulphuris calcareum.......sore nostrils, sneezing, running nose

Histaminum hydrochloricum......dries mucus membranes, sinus headache

Hydrastis canadensis...............profuse nasal discharge

Ignatia amara...........................headaches, tonsils inflamed, and swollen, dry cough

Kali bichromicum......................headaches, violent sneezing

Lemna minor............................dry throat, post-nasal dripping

Mercurius vivus........................thick mucus, runny nose, sneezing

Pulsatilla...................................itching, burning eyes, loss of smell, congestion and pain

Rhus toxicodendron..................headaches, face and throat pains

Sabadilla...................................sneezing, runny nose, sinus inflammation

Thuja occidentalis......................fever, tinnitus, vertigo

Reference image sinus.jpg

Warnings

If symptoms persist or worsen, or if pregnant or nursing, take only on advice of a healthcare professional. Keep out of reach of children.

Other Information

Tamper resistant for your protection. Use only if safety seal is intact.

Reference image sinus.jpg

OTC Keep Out Of Reach Of Children

Keep out of reach of children.

Reference image sinus.jpg

Indications and Usage

Uses temporarily relieves symptoms due to sinus discomforts associated with inflamed sinuses, hay fever or upper respiratory allergies:

- sinus pain and pressure
- runny nose
- sinus headaches
- sore throat
- nasal congestion
- dry mucus membranes
- sneezing
- itchy, burning eyes

Reference image sinus.jpg

PACKAGE LABEL

King Bio Inc.

3 Westside Drive

Asheville, NC 28806

www.kingbio.com

Reference image sinus.jpg